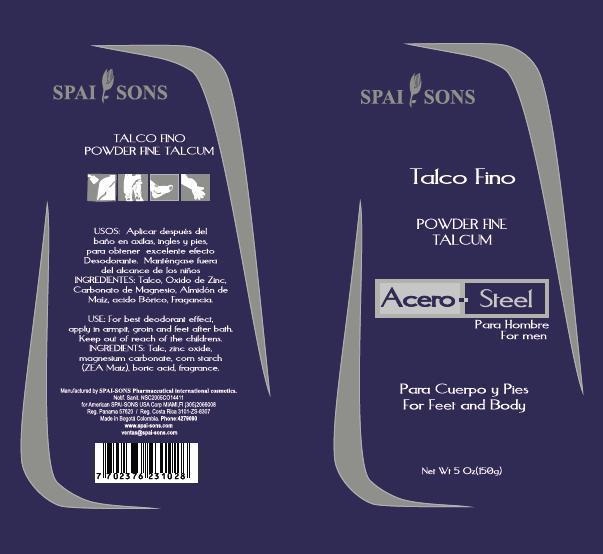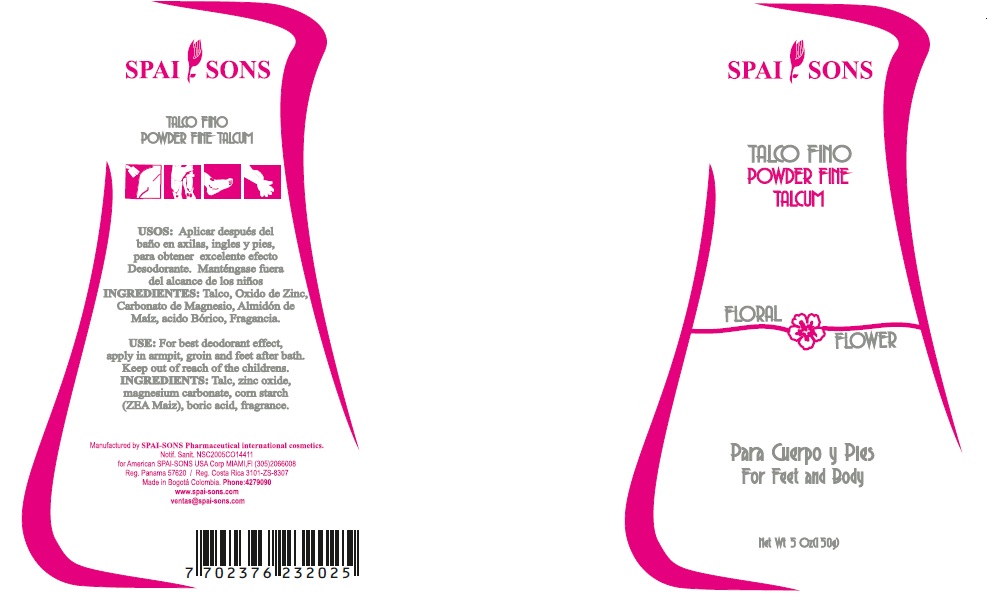 DRUG LABEL: SPAI-SONS
NDC: 66854-018 | Form: POWDER
Manufacturer: SPAI-SONS PHARMACEUTICAL INTERNATIONAL COSMETICS
Category: otc | Type: HUMAN OTC DRUG LABEL
Date: 20120605

ACTIVE INGREDIENTS: TALC 81 g/100 g; ZINC OXIDE 5 g/100 g
INACTIVE INGREDIENTS: MAGNESIUM CARBONATE; STARCH, CORN; BORIC ACID

SPAI-SONS TALCO FINO / POWDER FINE TALCUM

The active ingredient are Talc and Zinc Oxide

PURPOSE

This product is used to keep cool moist areas of the body as the feet and armpits, and retain moisture from them.

Keep out of reach of children this product

INDICATIONS AND USAGE

Use the product in the feet after the shower

WARNINGS

Do not take this product is only for topical application. If swallowed consult your doctor.

DOSAGE AND ADMINISTRATION

This product is for topical application, apply a moderate amount desired area.

Inactive ingredients not produce irritation or healt effects.

IMAGE OF THE LABEL